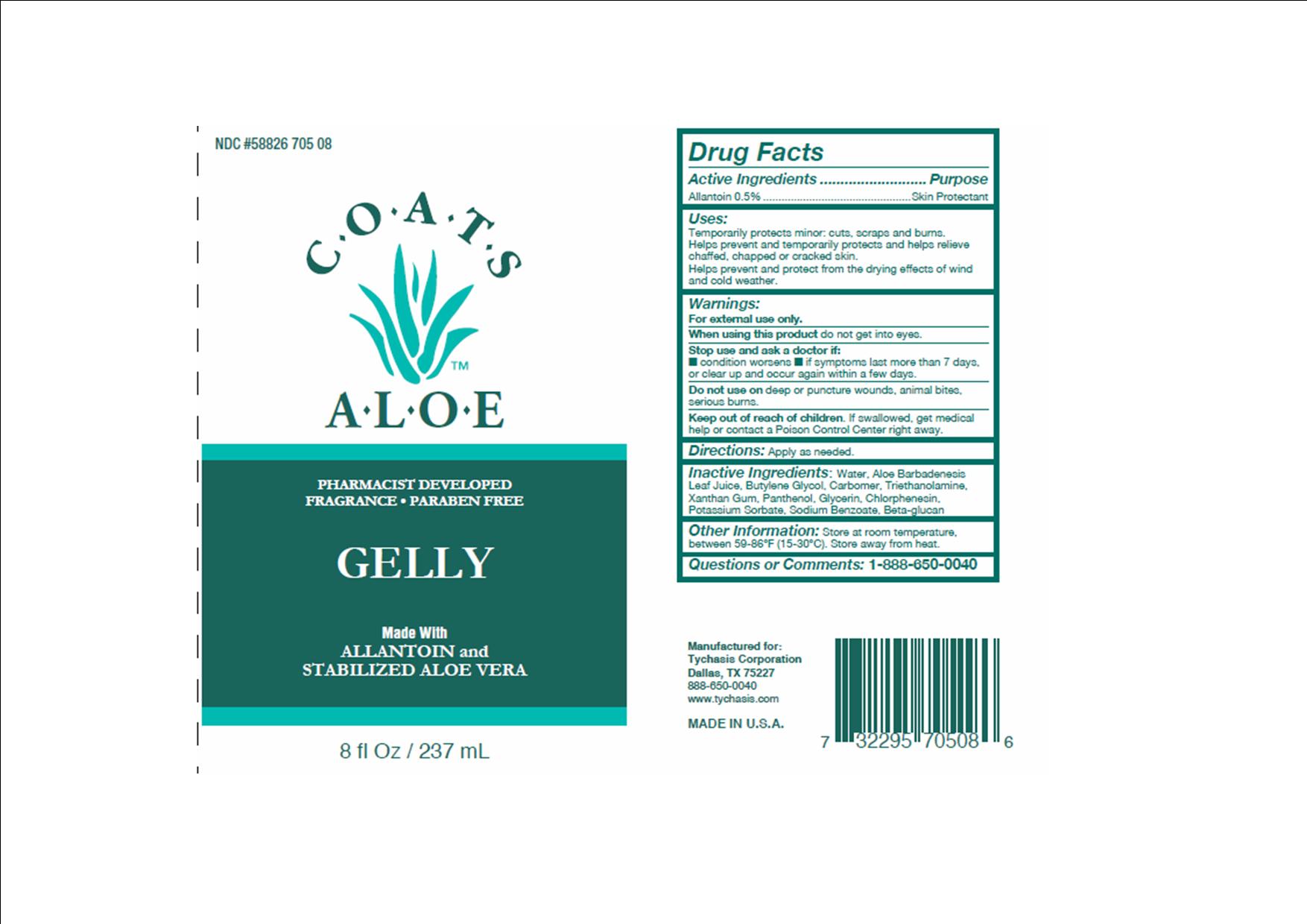 DRUG LABEL: COATS ALOE
NDC: 58826-705 | Form: JELLY
Manufacturer: TYCHASIS CORPORATION
Category: otc | Type: HUMAN OTC DRUG LABEL
Date: 20151009

ACTIVE INGREDIENTS: ALLANTOIN 0.5 g/100 mL
INACTIVE INGREDIENTS: CHLORPHENESIN; SODIUM BENZOATE; GLYCERIN; PANTHENOL; POTASSIUM SORBATE; WATER; ALOE VERA LEAF; BUTYLENE GLYCOL

COATS ALOE GELLY 90%

Active Ingredient

Allantoin 0.5%

Purpose

Skin protectant.

Warnings

For external use only.

When using this product do not get into eyes.

Uses:

Temporarily protects minor

- cuts
- scrapes
- burns

Helps prevent and temporarily protects and helps relieve chaffed, chapped or cracked skin.

Helps prevent and protect from the drying effects of wind and cold weather.

Stop use and ask a doctor if condition worsens, symptoms last more than 7 days, or clear up and occur again within a few days.

Inactive ingredients

aloe barbadenesis leaf juice, water, butylene glycol, carbomer, triethanolamine, xanthum gum, panthenol, glycerin, chlorphensin, potassium sorbate, sodium benzoate, beta-glucan

Directions

Apply as needed

Use

Apply as needed

Keep out of reach of children

If swallowed, get medical help or contact a Poison Control Center right away.

Do not use on deep puncture wounds, animal bits, serious burns.